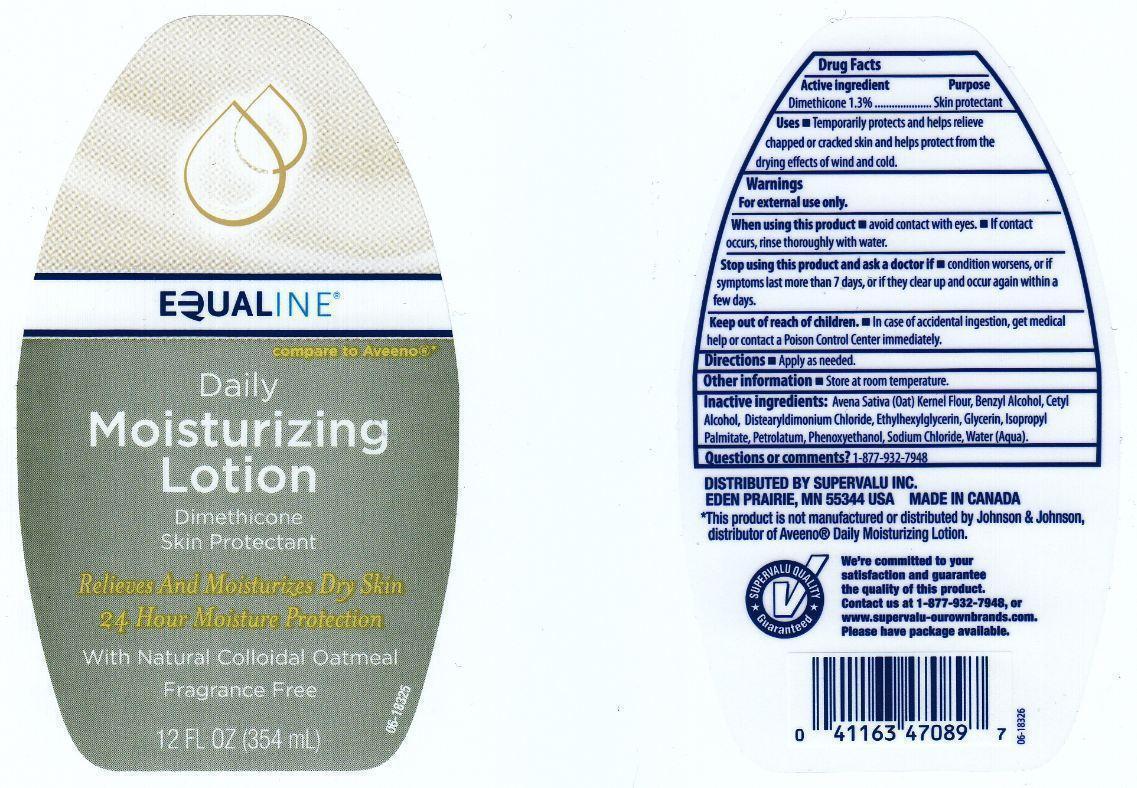 DRUG LABEL: EQUALINE
NDC: 41163-358 | Form: LOTION
Manufacturer: SUPERVALU INC.
Category: otc | Type: HUMAN OTC DRUG LABEL
Date: 20130115

ACTIVE INGREDIENTS: DIMETHICONE 13 mg/1 mL
INACTIVE INGREDIENTS: OATMEAL; BENZYL ALCOHOL; CETYL ALCOHOL; DISTEARYLDIMONIUM CHLORIDE; ETHYLHEXYLGLYCERIN; GLYCERIN; ISOPROPYL PALMITATE; PETROLATUM; PHENOXYETHANOL; SODIUM CHLORIDE; WATER

DRUG FACTS

ACTIVE INGREDIENT

DIMETHICONE 1.3%

PURPOSE

SKIN PROTECTANT

USES

TEMPORARILY PROTECTS AND HELPS RELIEVE CHAPPED OR CRACKED SKIN AND HELPS PROTECT FROM THE DRYING EFFECTS OF WIND AND COLD.

WARNINGS

FOR EXTERNAL USE ONLY.

WHEN USING THIS PRODUCT

AVOID CONTACT WITH EYES. IF CONTACT OCCURS, RINSE THOROUGHLY WITH WATER.

STOP USING THIS PRODUCT AND ASK A DOCTOR IF

CONDITION WORSENS, OR IF SYMPTOMS LAST MORE THAN 7 DAYS, OR IF THEY CLEAR UP AND OCCUR AGAIN WITHIN A FEW DAYS.

KEEP OUT OF REACH OF CHILDREN

IN CASE OF ACCIDENTAL INGESTION, GET MEDICAL HELP OR CONTACT A POISON CONTROL CENTER IMMEDIATELY.

DIRECTIONS

APPLY AS NEEDED.

OTHER INFORMATION

STORE AT ROOM TEMPERATURE.

INACTIVE INGREDIENTS:

AVENA SATIVA (OAT) KERNEL FLOUR, BENZYL ALCOHOL, CETYL ALCOHOL, DISTEARYLDIMONIUM CHLORIDE, ETHYLHEXYLGLYCERIN, GLYCERIN, ISOPROPYL PALMITATE, PETROLATUM, PHENOXYETHANOL, SODIUM CHLORIDE, WATER (AQUA).

QUESTIONS OR COMMENTS?

1-877-932-7948